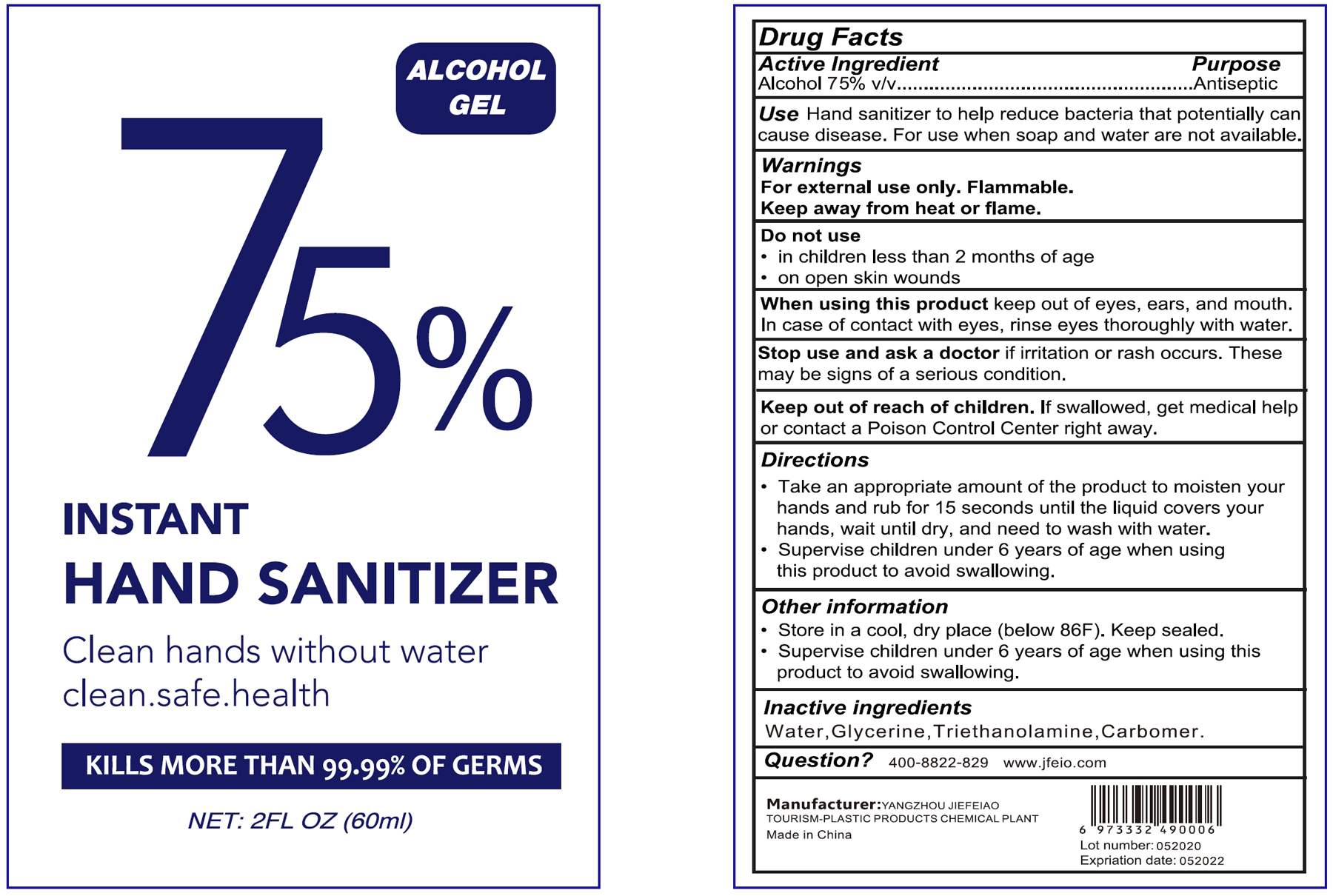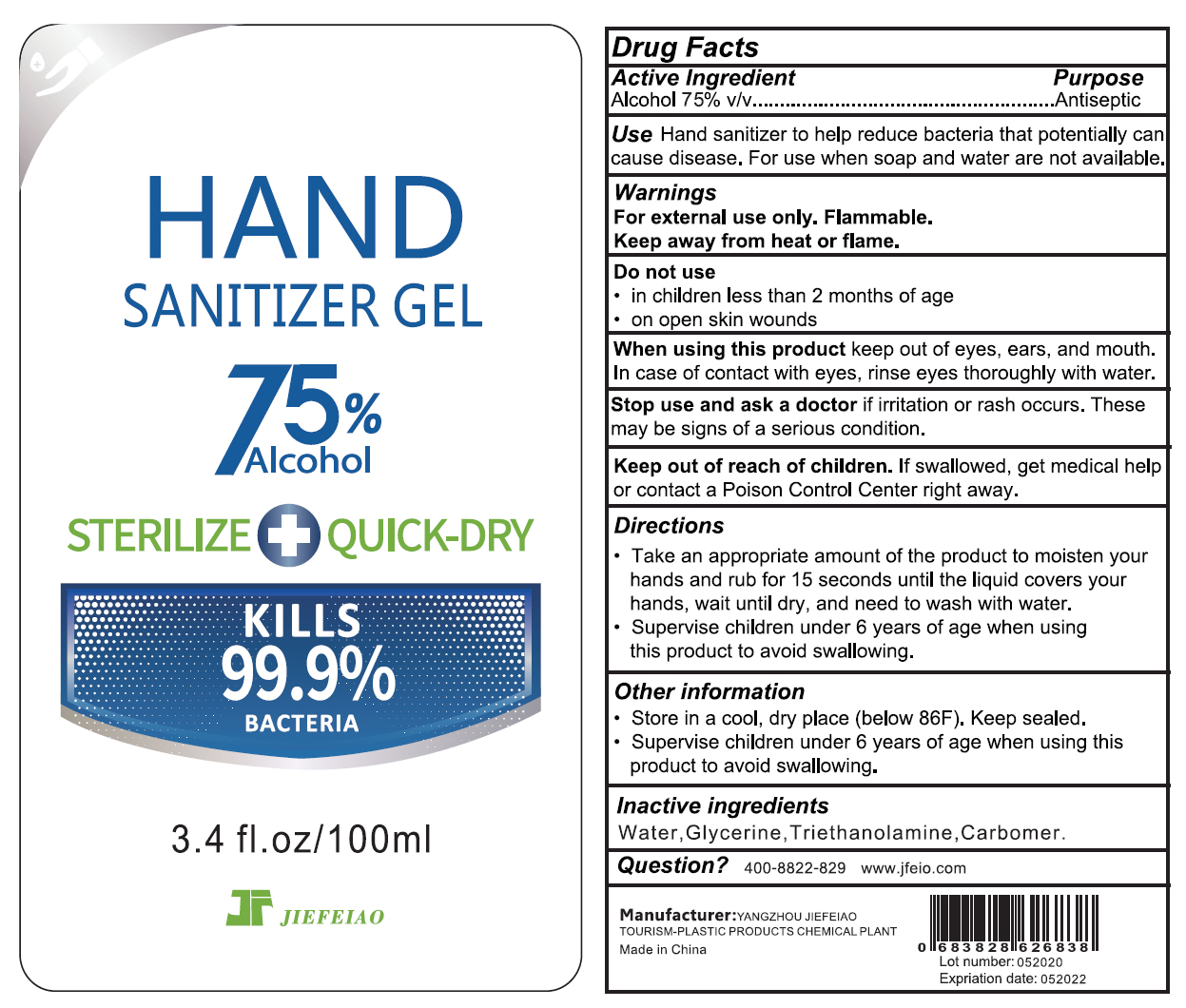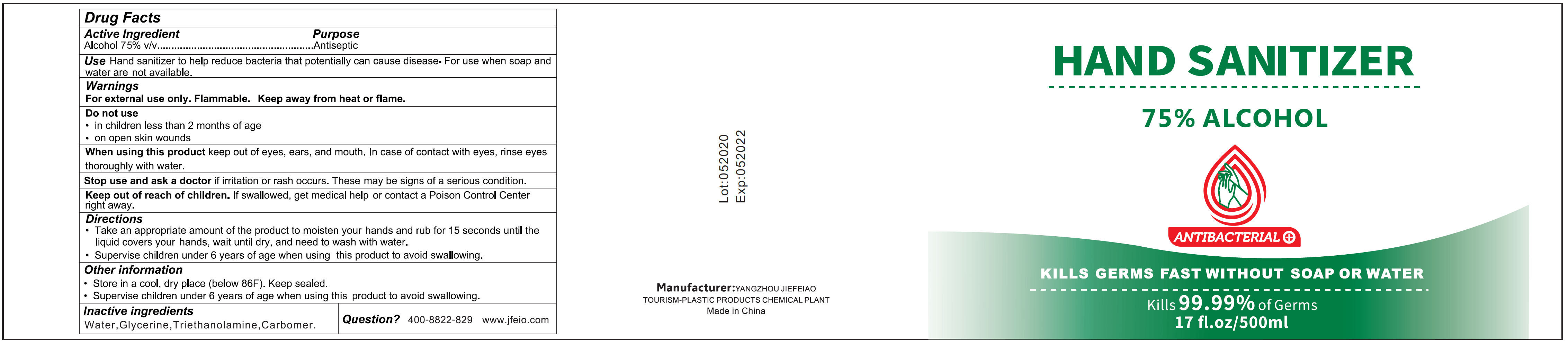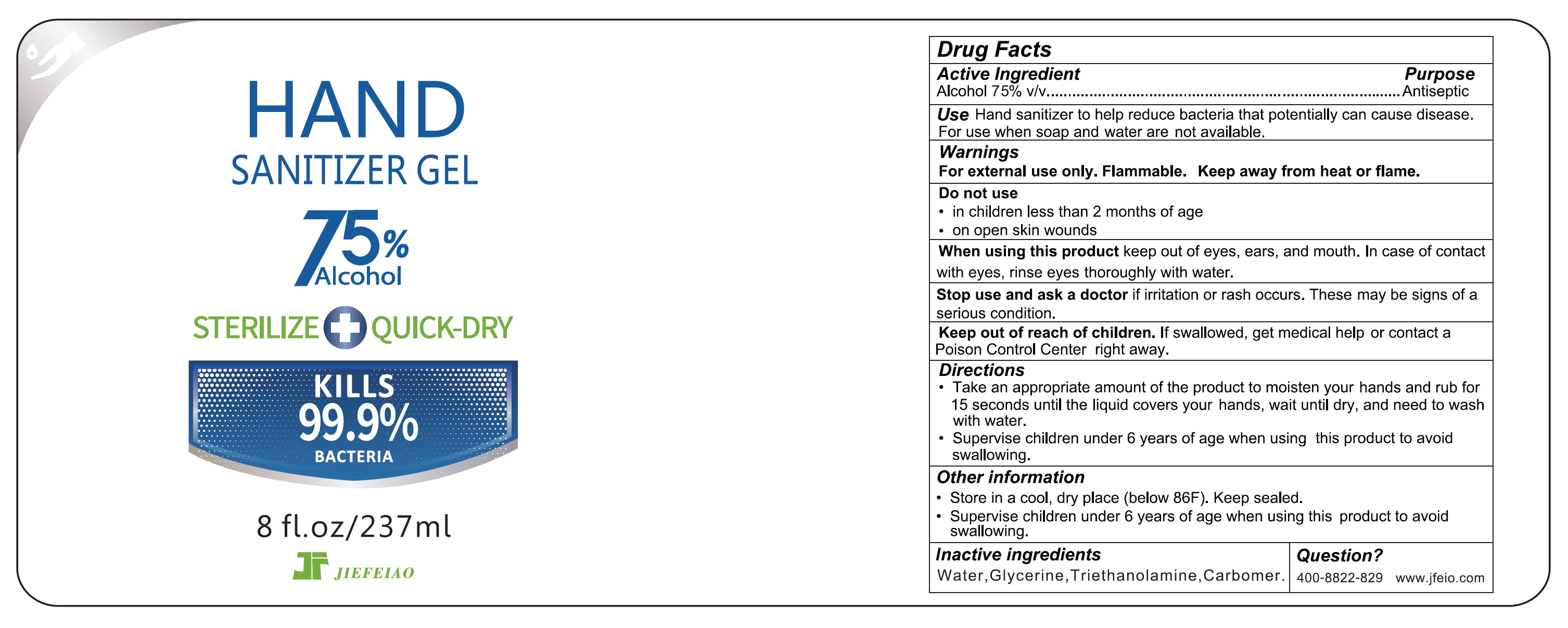 DRUG LABEL: Hand Sanitizer
NDC: 74742-003 | Form: GEL
Manufacturer: Yangzhou Jiefeiao Tourism-plastic Products Chemical Plant
Category: otc | Type: HUMAN OTC DRUG LABEL
Date: 20200618

ACTIVE INGREDIENTS: ALCOHOL 75 mL/100 mL
INACTIVE INGREDIENTS: CARBOMER HOMOPOLYMER, UNSPECIFIED TYPE; GLYCERIN; TROLAMINE; WATER

Hand Sanitizer Gel

Active Ingredient(s)

Alcohol 75% v/v. Purpose: Antiseptic

Purpose

Antiseptic, Hand Sanitizer

Use

Hand Sanitizer to help reduce bacteria that potentially can cause disease. For use when soap and water are not available.

Warnings

- For external use only. Flammable.
- Keep away from heat or flame

Do not use

- in children less than 2 months of age
- on open skin wounds

When using this product

keep out of eyes, ears, and mouth. In case of contact with eyes, rinse eyes thoroughly with water.

Stop use and ask a doctor

if irritation or rash occurs. These may be signs of a serious condition.

Keep out of reach of children. If swallowed, get medical help or contact a Poison Control Center right away.

Directions

- Take an appriopriate amount of the product to moisten your hands and rub for 15 seconds until the liquid covers your hands, wait until dry, and need to wash with water.
- Supervise children under 6 years of age when using this product to avoid swallowing.

Other information

- Store in a cool, dry place (below 86F). Keep sealed.
- Supervise children under 6 years of age when using this product to avoid swallowing.

Inactive ingredients

Water, Glycerin, Triethanolamine, Carbomer

Package Label - Principal Display Panel

60 mL NDC: 74742-003-01

100 mL NDC: 74742-003-02

500 mL NDC: 74742-003-03

237 mL NDC: 74742-003-04